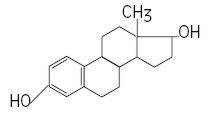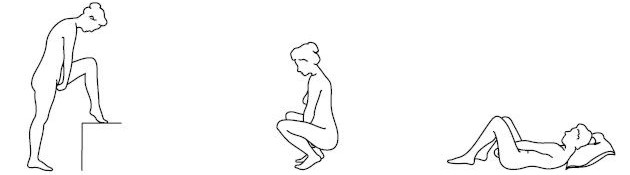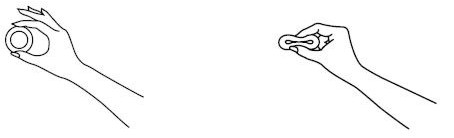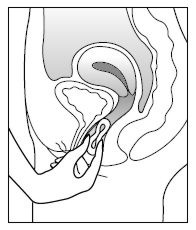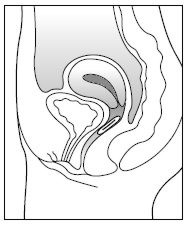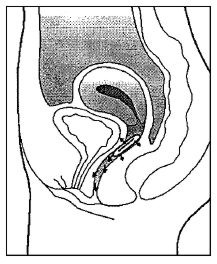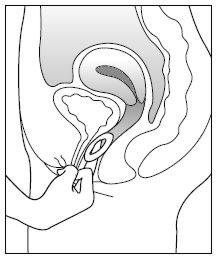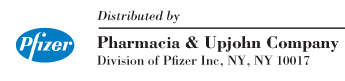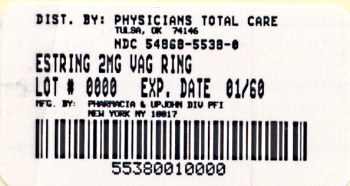 DRUG LABEL: Estring
NDC: 54868-5538 | Form: RING
Manufacturer: Physicians Total Care, Inc.
Category: prescription | Type: HUMAN PRESCRIPTION DRUG LABEL
Date: 20091001

ACTIVE INGREDIENTS: ESTRADIOL 2 mg/1 1
INACTIVE INGREDIENTS: BARIUM SULFATE

ESTRING®
(estradiol vaginal ring)

PHYSICIAN'S LEAFLET

WARNINGS

ENDOMETRIAL CANCER

Adequate diagnostic measures, including endometrial sampling when indicated, should be undertaken to rule out malignancy in all cases of undiagnosed persistent or recurring abnormal vaginal bleeding. (See WARNINGS, Malignant neoplasms, Endometrial cancer.)

CARDIOVASCULAR AND OTHER RISKS

Estrogens with or without progestins should not be used for the prevention of cardiovascular disease or dementia. (See CLINICAL STUDIES and WARNINGS, Cardiovascular disorders and Dementia.)

The Women's Health Initiative (WHI) estrogen alone substudy reported increased risks of stroke and deep vein thrombosis (DVT) in postmenopausal women (50 to 79 years of age) during 6.8 years and 7.1 years, respectively, of treatment with daily oral conjugated estrogens (CE 0.625 mg) relative to placebo. (See CLINICAL STUDIES and WARNINGS, Cardiovascular disorders.)

The estrogen plus progestin WHI substudy reported increased risks of myocardial infarction, stroke, invasive breast cancer, pulmonary emboli, and DVT in postmenopausal women (50 to 79 years of age) during 5.6 years of treatment with daily oral CE 0.625 mg combined with medroxyprogesterone acetate (MPA 2.5 mg), relative to placebo. (See CLINICAL STUDIES and WARNINGS, Cardiovascular disorders and Malignant neoplasms, Breast cancer.)

The Women's Health Initiative Memory Study (WHIMS), a substudy of the WHI, reported increased risk of developing probable dementia in postmenopausal women 65 years of age or older during 5.2 years of treatment with daily CE 0.625 mg alone and during 4 years of treatment with daily CE 0.625 mg combined with MPA 2.5 mg, relative to placebo. It is unknown whether this finding applies to younger postmenopausal women. (See CLINICAL STUDIES and WARNINGS, Dementia and PRECAUTIONS, Geriatric Use.)

In the absence of comparable data, these risks should be assumed to be similar for other doses of CE and MPA and other combinations and dosage forms of estrogens and progestins. Because of these risks, estrogens with or without progestins should be prescribed at the lowest effective doses and for the shortest duration consistent with treatment goals and risks for the individual woman.

DESCRIPTION

ESTRING® (estradiol vaginal ring) is a slightly opaque ring with a whitish core containing a drug reservoir of 2 mg estradiol. Estradiol, silicone polymers and barium sulfate are combined to form the ring. When placed in the vagina, ESTRING releases estradiol, approximately 7.5 mcg per 24 hours, in a consistent stable manner over 90 days. ESTRING has the following dimensions: outer diameter 55 mm; cross-sectional diameter 9 mm; core diameter 2 mm. One ESTRING should be inserted into the upper third of the vaginal vault, to be worn continuously for three months.

Estradiol is chemically described as estra-1,3,5(10)-triene-3,17β-diol. The molecular formula of estradiol is C18H24O2 and the structural formula is:

The molecular weight of estradiol is 272.39.

CLINICAL PHARMACOLOGY

Endogenous estrogens are largely responsible for the development and maintenance of the female reproductive system and secondary sexual characteristics. Although circulating estrogens exist in a dynamic equilibrium of metabolic interconversions, estradiol is the principal intracellular human estrogen and is substantially more potent than its metabolites, estrone and estriol, at the receptor level.

The primary source of estrogen in normally cycling adult women is the ovarian follicle, which secretes 70 to 500 mcg of estradiol daily, depending on the phase of the menstrual cycle. After menopause, most endogenous estrogen is produced by conversion of androstenedione, secreted by the adrenal cortex, to estrone by peripheral tissues. Thus, estrone and the sulfate conjugated form, estrone sulfate, are the most abundant circulating estrogens in postmenopausal women.

Estrogens act through binding to nuclear receptors in estrogen-responsive tissues. To date, two estrogen receptors have been identified. These vary in proportion from tissue to tissue.

Circulating estrogens modulate the pituitary secretion of the gonadotropins, luteinizing hormone (LH) and follicle stimulating hormone (FSH), through a negative feedback mechanism. Estrogens act to reduce the elevated levels of these hormones seen in postmenopausal women.

Pharmacokinetics

A. Absorption

Estrogens used in therapeutics are well absorbed through the skin, mucous membranes, and the gastrointestinal (GI) tract. The vaginal delivery of estrogens circumvents first-pass metabolism.

In a Phase I study of 14 postmenopausal women, the insertion of ESTRING (estradiol vaginal ring) rapidly increased serum estradiol (E2) levels. The time to attain peak serum estradiol levels (Tmax) was 0.5 to 1 hour. Peak serum estradiol concentrations post-initial burst declined rapidly over the next 24 hours and were virtually indistinguishable from the baseline mean (range: 5 to 22 pg/mL). Serum levels of estradiol and estrone (E1) over the following 12 weeks during which the ring was maintained in the vaginal vault remained relatively unchanged (see Table 1).

The initial estradiol peak post-application of the second ring in the same women resulted in ~38 percent lower Cmax, apparently due to reduced systemic absorption via the treated vaginal epithelium. The relative systemic exposure from the initial peak of ESTRING accounted for approximately 4 percent of the total estradiol exposure over the 12-week period.

The release of estradiol from ESTRING was demonstrated in a Phase II study of 222 postmenopausal women who inserted up to four rings consecutively at three-month intervals. Systemic delivery of estradiol from ESTRING resulted in mean steady state serum estradiol estimates of 7.8, 7.0, 7.0, 8.1 pg/mL at weeks 12, 24, 36, and 48, respectively. Similar reproducibility is also seen in levels of estrone. The systemic exposure to estradiol and estrone was within the range observed in untreated women after the first eight hours.

In postmenopausal women, mean dose of estradiol systemically absorbed unchanged from ESTRING is ~8 percent [95 percent CI: 2.8–12.8 percent] of the daily amount released locally.

TABLE 1: PHARMACOKINETIC MEAN ESTIMATES FOLLOWING SINGLE ESTRING APPLICATION
Estrogen | Cmax (pg/mL) | Css–48 hr (pg/mL) | Css–4w (pg/mL) | Css–12w (pg/mL)
Estradiol (E2) | 63.2 [n=14] | 11.2 | 9.5 | 8.0
Baseline-adjusted E2 [Based on means] | 55.6 | 3.6 | 2.0 | 0.4
Estrone (E1) | 66.3 | 52.5 | 43.8 | 47.0
Baseline-adjusted E1 | 20.0 | 6.2 | -2.4 | 0.8

B. Distribution

The distribution of exogenous estrogens is similar to that of endogenous estrogens. Estrogens are widely distributed in the body and are generally found in higher concentrations in the sex hormone target organs. Estrogens circulate in the blood largely bound to sex hormone binding globulin (SHBG) and albumin.

C. Metabolism

Exogenous estrogens are metabolized in the same manner as endogenous estrogens. Circulating estrogens exist in a dynamic equilibrium of metabolic interconversions. These transformations take place mainly in the liver. Estradiol is converted reversibly to estrone, and both can be converted to estriol, which is the major urinary metabolite. Estrogens also undergo enterohepatic recirculation via sulfate and glucuronide conjugation in the liver, biliary secretion of conjugates into the intestine, and hydrolysis in the intestine followed by reabsorption. In postmenopausal women, a significant proportion of the circulating estrogens exist as sulfate conjugates, especially estrone sulfate, which serves as a circulating reservoir for the formation of more active estrogens.

D. Excretion

Estradiol, estrone, and estriol are excreted in the urine along with glucuronide and sulfate conjugates.

Mean percent dose excreted in the 24-hour urine as estradiol, 4 and 12 weeks post-application of ESTRING in a Phase I study was 5 percent and 8 percent, respectively, of the daily released amount.

E. Special Populations

ESTRING has not been studied in patients with hepatic or renal impairment.

F. Drug Interactions

No formal drug interactions studies have been done with ESTRING.

In vitro and in vivo studies have shown that systemic estrogens are metabolized partially by cytochrome P450 3A4 (CYP3A4). Therefore, inducers or inhibitors of CYP3A4 may affect estrogen metabolism. Inducers of CYP3A4 such as St. John's Wort preparations (Hypericum perforatum), phenobarbital, carbamazepine, and rifampin may reduce plasma concentrations of estrogens, possibly resulting in a decrease in systemic effects and/or changes in the uterine bleeding profile. Inhibitors of CYP3A4 such as erythromycin, clarithromycin, ketoconazole, itraconazole, ritonavir and grapefruit juice may increase plasma concentrations of estrogens and may result in side effects.

CLINICAL STUDIES

Effects on vulvar and vaginal atrophy

Two pivotal controlled studies have demonstrated the efficacy of ESTRING (estradiol vaginal ring) in the treatment of postmenopausal urogenital symptoms due to estrogen deficiency.

In a U.S. study where ESTRING was compared with conjugated estrogens vaginal cream, no difference in efficacy between the treatment groups was found with respect to improvement in the physician's global assessment of vaginal symptoms (83 percent and 82 percent of patients receiving ESTRING and cream, respectively) and in the patient's global assessment of vaginal symptoms (83 percent and 82 percent of patients receiving ESTRING and cream, respectively) after 12 weeks of treatment. In an Australian study, ESTRING was also compared with conjugated estrogens vaginal cream and no difference in the physician's assessment of improvement of vaginal mucosal atrophy (79 percent and 75 percent for ESTRING and cream, respectively) or in the patient's assessment of improvement in vaginal dryness (82 percent and 76 percent for ESTRING and cream, respectively) after 12 weeks of treatment.

In the U.S. study, symptoms of dysuria and urinary urgency improved in 74 percent and 65 percent, respectively, of patients receiving ESTRING as assessed by the patient. In the Australian study, symptoms of dysuria and urinary urgency improved in 90 percent and 71 percent, respectively, of patients receiving ESTRING as assessed by the patient.

In both studies, ESTRING and conjugated estrogens vaginal cream had a similar ability to reduce vaginal pH levels and to mature the vaginal mucosa (as measured cytologically using the maturation index and/or the maturation value) after 12 weeks of treatment. In supportive studies, ESTRING was also shown to have a similar significant treatment effect on the maturation of the urethral mucosa.

Endometrial overstimulation, as evaluated in non-hysterectomized patients participating in the U.S. study by the progestogen challenge test and pelvic sonogram, was reported for none of the 58 (0 percent) patients receiving ESTRING and 4 of the 35 patients (11 percent) receiving conjugated estrogens vaginal cream.

Of the U.S. women who completed 12 weeks of treatment, 95 percent rated product comfort for ESTRING as excellent or very good compared with 65 percent of patients receiving conjugated estrogens vaginal cream, 95 percent of ESTRING patients judged the product to be very easy or easy to use compared with 88 percent of cream patients, and 82 percent gave ESTRING an overall rating of excellent or very good compared with 58 percent for the cream.

Women's Health Initiative Studies

The Women's Health Initiative (WHI) enrolled approximately 27,000 predominantly healthy postmenopausal women in two substudies to assess the risks and benefits of either the use of daily oral conjugated estrogens (CE 0.625 mg) alone or in combination with medroxyprogesterone acetate (MPA 2.5 mg) compared to placebo in the prevention of certain chronic diseases. The primary endpoint was the incidence of coronary heart disease (CHD) (nonfatal myocardial infarction [MI], silent MI and CHD death), with invasive breast cancer as the primary adverse outcome studied. A "global index" included the earliest occurrence of CHD, invasive breast cancer, stroke, pulmonary embolism (PE), endometrial cancer (only in the CE/MPA substudy), colorectal cancer, hip fracture, or death due to other cause. These substudies did not evaluate the effects of CE or CE/MPA on menopausal symptoms.

The estrogen alone substudy was stopped early because an increased risk of stroke was observed and it was deemed that no further information would be obtained regarding the risks and benefits of estrogen alone in predetermined primary endpoints. Results of the estrogen alone substudy, which included 10,739 women (average age 63 years, range 50 to 79; 75.3 percent White, 15.1 percent Black, 6.1 percent Hispanic, 3.6 percent Other), after an average follow-up of 6.8 years are presented in Table 2.

TABLE 2: RELATIVE AND ABSOLUTE RISK SEEN IN THE ESTROGEN ALONE SUBSTUDY OF WHI
Event | Relative Risk CE vs. Placebo (95% nCI [Nominal confidence intervals unadjusted for multiple looks and multiple comparisons.]) | Placebo n = 5,429 | CE n = 5,310
Event | Relative Risk CE vs. Placebo (95% nCI [Nominal confidence intervals unadjusted for multiple looks and multiple comparisons.]) | Absolute Risk per 10,000 Women-Years
CHD events [Results are based on centrally adjudicated data for an average follow-up of 7.1 years.] | 0.95 (0.79–1.16) | 56 | 53
Nonfatal MI | 0.91 (0.73–1.14) | 43 | 40
CHD death | 1.01 (0.71–1.43) | 16 | 16
Stroke | 1.37 (1.09–1.73) | 33 | 45
Ischemic | 1.55 (1.19–2.01) | 25 | 38
Deep vein thrombosis, [Not included in Global index.] | 1.47 (1.06–2.06) | 15 | 23
Pulmonary embolism | 1.37 (0.90–2.07) | 10 | 14
Invasive breast cancer | 0.80 (0.62–1.04) | 34 | 28
Colorectal cancer [Results are based on an average follow-up of 6.8 years.] | 1.08 (0.75–1.55) | 16 | 17
Hip fracture | 0.61 (0.41–0.91) | 17 | 11
Vertebral fractures, | 0.62 (0.42–0.93) | 17 | 11
Total fractures, | 0.70 (0.63–0.79) | 195 | 139
Death due to other causes, [All deaths, except from breast or colorectal cancer, definite/probable CHD, PE or cerebrovascular disease.] | 1.08 (0.88–1.32) | 50 | 53
Overall mortality, | 1.04 (0.88–1.22) | 78 | 81
Global index, [A subset of the events was combined in a "global index" defined as the earliest occurrence of CHD events, invasive breast cancer, stroke, pulmonary embolism, endometrial cancer, colorectal cancer, hip fracture, or death due to other causes.] | 1.01 (0.91–1.12) | 190 | 192

For those outcomes included in the WHI "global index" that reached statistical significance, the absolute excess risk per 10,000 women-years in the group treated with CE alone was 12 more strokes, while the absolute risk reduction per 10,000 women-years was 6 fewer hip fractures. The absolute excess risk of events included in the "global index" was a nonsignificant 2 events per 10,000 women-years. There was no difference between the groups in terms of all-cause mortality. (See BOXED WARNINGS, WARNINGS, and PRECAUTIONS.)

Final centrally adjudicated results for CHD events and centrally adjudicated results for invasive breast cancer incidence from the estrogen alone substudy, after an average follow-up of 7.1 years, reported no overall difference from primary CHD events (nonfatal MI, silent MI and CHD death) and invasive breast cancer incidence in women receiving CE alone compared with placebo (see Table 2).

Centrally adjudicated results for stroke events from the estrogen alone substudy, after an average follow-up of 7.1 years, reported no significant differences in distribution of stroke subtypes or severity, including fatal strokes, in women receiving CE alone compared to placebo. Estrogen alone increased the risk for ischemic stroke, and this excess risk was present in all subgroups of women examined (see Table 2).

The estrogen plus progestin substudy was also stopped early. According to the predefined stopping rule, after an average follow-up of 5.2 years of treatment, the increased risk of breast cancer and cardiovascular events exceeded the specified benefits included in the "global index." The absolute excess risk of events included in the "global index" was 19 per 10,000 women-years (relative risk [RR] 1.15, 95 percent nCI 1.03–1.28).

For those outcomes included in the WHI "global index" that reached statistical significance after 5.6 years of follow-up, the absolute excess risks per 10,000 women-years in the group treated with CE/MPA were 6 more CHD events, 7 more strokes, 10 more PEs, and 8 more invasive breast cancers, while the absolute risk reductions per 10,000 women-years were 7 fewer colorectal cancers and 5 fewer hip fractures. (See BOXED WARNINGS, WARNINGS, and PRECAUTIONS.)

Results of the estrogen plus progestin substudy, which included 16,608 women (average of 63 years, range 50 to 79; 83.9 percent White, 6.8 percent Black, 5.4 percent Hispanic, 3.9 percent Other), are presented in Table 3. These results reflect centrally adjudicated data after an average follow-up of 5.6 years.

TABLE 3: RELATIVE AND ABSOLUTE RISK SEEN IN THE ESTROGEN PLUS PROGESTIN SUBSTUDY OF WHI AT AN AVERAGE OF 5.6 YEARS [Results are based on centrally adjudicated data. Mortality data was not part of the adjudicated data; however, data at 5.2 years of follow-up showed no difference between the groups in terms of all-cause mortality (RR 0.98, 95 percent nCI, 0.82–1.18).]
Event | Relative Risk CE/MPA vs. placebo (95% nCI [Nominal confidence intervals unadjusted for multiple looks and multiple comparisons.]) | Placebo n = 8,102 | CE/MPA n = 8,506
Event | Relative Risk CE/MPA vs. placebo (95% nCI [Nominal confidence intervals unadjusted for multiple looks and multiple comparisons.]) | Absolute Risk per 10,000 Women-Years
CHD events | 1.24 (1.00–1.54) | 33 | 39
Nonfatal MI | 1.28 (1.00–1. 63) | 25 | 31
CHD death | 1.10 (0.70–1.75) | 8 | 8
All strokes | 1.31 (1.02–1.68) | 24 | 31
Ischemic Stroke | 1.44 (1.09–1.90) | 18 | 26
Deep vein thrombosis | 1.95 (1.43–2.67) | 13 | 26
Pulmonary embolism | 2.13 (1.45–3.11) | 8 | 18
Invasive breast cancer [Includes metastasis and non-metastatic breast cancer, with the exception of in situ breast cancer.] | 1.24 (1.01–1.54) | 33 | 41
Invasive colorectal cancer | 0.56 (0.38–0.81) | 16 | 9
Endometrial cancer | 0.81 (0.48–1.36) | 7 | 6
Cervical cancer | 1.44 (0.47–4.42) | 1 | 2
Hip fracture | 0.67 (0.47–0.96) | 16 | 11
Vertebral fracture | 0.65 (0.46–0.92) | 17 | 11
Lower arm/wrist fractures | 0.71 (0.59–0.85) | 62 | 44
Total fractures | 0.76 (0.69–0.83) | 199 | 152

Women's Health Initiative Memory Study

The estrogen alone Women's Health Initiative Memory Study (WHIMS), a substudy of the WHI, enrolled 2,947 predominantly healthy postmenopausal women 65 years of age and older (45 percent were 65 to 69 years of age, 36 percent were 70 to 74 years of age, and 19 percent were 75 years of age and older) to evaluate the effects of daily conjugated estrogens (CE 0.625 mg) on the incidence of probable dementia (primary outcome) compared with placebo.

After an average follow-up of 5.2 years, 28 women in the estrogen alone group (37 per 10,000 women-years) and 19 in the placebo group (25 per 10,000 women-years) were diagnosed with probable dementia. The relative risk of probable dementia in the estrogen alone group was 1.49 (95 percent CI, 0.83–2.66) compared to placebo. It is unknown whether these findings apply to younger postmenopausal women. (See BOXED WARNINGS, WARNINGS, Dementia, and PRECAUTIONS, Geriatric Use.)

The estrogen plus progestin WHIMS substudy enrolled 4,532 predominantly healthy postmenopausal women 65 years of age and older (47 percent were 65 to 69 years of age, 35 percent were 70 to 74 years of age, and 18 percent were 75 years of age and older) to evaluate the effects of daily CE 0.625 mg plus medroxyprogesterone acetate (MPA 2.5 mg) on the incidence of probable dementia (primary outcome) compared with placebo.

After an average follow-up of 4 years, 40 women in the estrogen plus progestin group (45 per 10,000 women-years) and 21 in the placebo group (22 per 10,000 women-years) were diagnosed with probable dementia. The relative risk of probable dementia in the hormone therapy group was 2.05 (95 percent CI, 1.21–3.48) compared to placebo.

When data from the two populations were pooled as planned in the WHIMS protocol, the reported overall relative risk for probable dementia was 1.76 (95 percent CI, 1.19–2.60). Differences between groups became apparent in the first year of treatment. It is unknown whether these findings apply to younger postmenopausal women. (See BOXED WARNING, WARNINGS, Dementia, and PRECAUTIONS, Geriatric Use.)

INDICATIONS AND USAGE

ESTRING (estradiol vaginal ring) is an estrogen indicated for the treatment of moderate to severe urogenital symptoms due to postmenopausal atrophy of the vagina (such as dryness, burning, pruritus and dyspareunia) and/or the lower urinary tract (urinary urgency and dysuria).

CONTRAINDICATIONS

ESTRING vaginal ring should not be used in women with any of the following conditions:

1. Undiagnosed abnormal genital bleeding.
2. Known, suspected, or history of cancer of the breast.
3. Known or suspected estrogen-dependent neoplasia.
4. Active deep vein thrombosis, pulmonary embolism or a history of these conditions.
5. Active or recent (within the past year) arterial thromboembolic disease (for example, stroke and myocardial infarction).
6. Known liver dysfunction or disease.
7. Known hypersensitivity to any of the ingredients in ESTRING.
8. Known or suspected pregnancy.

WARNINGS

See BOXED WARNINGS

ESTRING is a vaginal administered product with low systemic absorption following continuous use for 3 months (see CLINICAL PHARMACOLOGY, Pharmacokinetics, Absorption). The estrogen plus progestin substudy of WHI utilized systemically-absorbed oral estrogen/progestin. However, the warnings, precautions, and adverse reactions associated with oral estrogen and/or progestin therapy should be considered in the absence of comparable data with other dosage forms of estrogens and/or progestins.

1. Cardiovascular disorders

An increased risk of stroke and deep vein thrombosis (DVT) has been reported with estrogen alone therapy. An increased risk of stroke, DVT, pulmonary embolism, and myocardial infarction has been reported with estrogen plus progestin therapy. Should any of these occur or be suspected, estrogens with or without progestins should be discontinued immediately.

Risk factors for arterial vascular disease (for example, hypertension, diabetes mellitus, tobacco use, hypercholesterolemia, and obesity) and/or venous thromboembolism (VTE) (for example, personal history or family history of VTE, obesity, and systemic lupus erythematosus) should be managed appropriately.

a. Stroke

In the Women's Health Initiative (WHI), estrogen alone substudy, a statistically significant increased risk of stroke was reported in women receiving daily conjugated estrogens (CE 0.625 mg) compared to placebo (45 versus 33 per 10,000 women-years). The increase in risk was demonstrated in year one and persisted. (See CLINICAL STUDIES.)

In the estrogen plus progestin substudy of WHI, a statistically significant increased risk of stroke was reported in women receiving daily CE 0.625 mg plus medroxyprogesterone acetate (MPA 2.5 mg) compared to placebo (31 versus 24 per 10,000 women-years). The increase in risk was demonstrated after the first year and persisted. (See CLINICAL STUDIES.)

b. Coronary heart disease

In the estrogen alone substudy of WHI, no overall effect on coronary heart disease (CHD) events (defined as nonfatal myocardial infarction [MI], silent MI and CHD death) was reported in women receiving estrogen alone compared to placebo. (See CLINICAL STUDIES.)

In the estrogen plus progestin substudy of WHI, no statistically significant increase of CHD events was reported in women receiving CE/MPA compared to women receiving placebo (39 versus 33 per 10,000 women-years). An increase in relative risk was demonstrated in year 1, and a trend toward decreasing relative risk was reported in years 2 through 5. (See CLINICAL STUDIES.)

In postmenopausal women with documented heart disease (n = 2,763, average age 66.7 years), in a controlled clinical trial of secondary prevention of cardiovascular disease (Heart and Estrogen/Progestin Replacement Study [HERS]) treatment with daily CE 0.625 mg/MPA 2.5 mg demonstrated no cardiovascular benefit. During an average follow-up of 4.1 years, treatment with CE/MPA did not reduce the overall rate of CHD events in postmenopausal women with established coronary heart disease. There were more CHD events in the CE/MPA-treated group than in the placebo group in year one, but not during the subsequent years. Two thousand three hundred and twenty-one (2,321) women from the original HERS trial agreed to participate in an open label extension of HERS, HERS II. Average follow-up in HERS II was an additional 2.7 years, for a total of 6.8 years overall. Rates of CHD events were comparable among women in the combined continuous CE/MPA treatment group and the placebo group in HERS, HERS II, and overall.

c. Venous thromboembolism (VTE)

In the estrogen alone substudy of WHI, the risk of VTE (DVT and pulmonary embolism [PE]) was reported to be increased for women receiving daily CE compared to women receiving placebo (30 versus 22 per 10,000 women-years), although only the increased risk of DVT reached statistical significance (23 versus 15 per 10,000 women-years). The increase in VTE risk was demonstrated during the first two years. (See CLINICAL STUDIES.)

In the estrogen plus progestin substudy of WHI, a statistically significant two-fold greater rate of VTE was reported in women receiving daily CE/MPA compared to women receiving placebo (35 versus 17 per 10,000 women-years). Statistically significant increases in risk for both DVT (26 versus 13 per 10,000 women-years) and PE (18 versus 8 per 10,000 women-years) were also demonstrated. The increase in VTE risk was observed during the first year and persisted. (See CLINICAL STUDIES.)

If feasible, estrogens should be discontinued at least 4 to 6 weeks before surgery of the type associated with an increased risk of thromboembolism, or during periods of prolonged immobilization.

2. Malignant neoplasms

a. Endometrial cancer

An increased risk of endometrial cancer has been reported with the use of unopposed estrogen therapy in women with a uterus. The reported endometrial cancer risk among unopposed estrogen users is about 2 to 12-times greater than in nonusers, and appears dependent on duration of treatment and on estrogen dose. Most studies show no significant increased risk associated with use of estrogens for less than 1 year. The greatest risk appears associated with prolonged use, with increased risks of 15 to 24-fold for 5 to 10 years or more. This risk has been shown to persist for at least 8 to 15 years after estrogen therapy is discontinued.

Clinical surveillance of all women taking estrogen plus progestin therapy is important. Adequate diagnostic measures, including endometrial sampling when indicated, should be undertaken to rule out malignancy in all cases of undiagnosed persistent or recurring abnormal vaginal bleeding. There is no evidence that the use of natural estrogens result in a different endometrial risk profile than synthetic estrogens of equivalent estrogen dose. Adding a progestin to estrogen therapy has been shown to reduce the risk of endometrial hyperplasia, which may be a precursor to endometrial cancer.

b. Breast cancer

The use of estrogens and progestins by postmenopausal women has been reported to increase the risk of breast cancer in some studies. Observational studies have also reported an increased risk of breast cancer for estrogen plus progestin therapy, and a smaller increased risk for estrogen alone therapy, after several years of use. The risk increased with duration of use, and appeared to return to baseline over about 5 years after stopping treatment (only the observational studies have substantial data on risk after stopping). Observational studies also suggest that the risk of breast cancer was greater, and became apparent earlier, with estrogen plus progestin therapy as compared to estrogen alone therapy. However, these studies have not found significant variation in the risk of breast cancer among different estrogen plus progestin combinations, doses, or routes of administration.

The most important randomized clinical trial providing information about this issue is the Women Health Initiative (WHI) substudy of daily conjugated estrogens (CE 0.625 mg) plus medroxyprogesterone acetate (MPA 2.5 mg) (see CLINICAL STUDIES). In the estrogen alone substudy of WHI, after an average of 7.1 years of follow-up, daily CE 0.625 mg was not associated with an increased risk of invasive breast cancer (relative risk [RR] 0.80, 95 percent nominal confidence interval [nCI] 0.62–1.04).

In the estrogen plus progestin substudy, after a mean follow-up of 5.6 years, the WHI substudy reported an increased risk of breast cancer in women who took daily CE/MPA. In this substudy, prior use of estrogen alone or estrogen plus progestin therapy was reported by 26 percent of the women. The relative risk of invasive breast cancer was 1.24 (95 percent nCI, 1.01–1.54), and the absolute risk was 41 versus 33 cases per 10,000 women-years, for estrogen plus progestin compared with placebo, respectively. Among women who reported prior use of hormone therapy, the relative risk of invasive breast cancer was 1.86, and the absolute risk was 46 versus 25 cases per 10,000 women-years, for CE/MPA compared with placebo. Among women who reported no prior use of hormone therapy, the relative risk of invasive breast cancer was 1.09, and the absolute risk was 40 versus 36 per 10,000 women-years for estrogen plus progestin compared with placebo. In the same substudy, invasive breast cancers were larger and diagnosed at a more advanced stage in the CE/MPA group compared with the placebo group. Metastatic disease was rare with no apparent difference between the two groups. Other prognostic factors such as histologic subtype, grade, and hormone receptor status did not differ between the groups.

The use of estrogen alone and estrogen plus progestin has been reported to result in an increase in abnormal mammograms requiring further evaluation. All women should receive yearly breast exams by a healthcare provider and perform monthly self-examinations. In addition, mammography examinations should be scheduled based on patient age, risk factors, and prior mammogram results.

c. Ovarian cancer

The estrogen plus progestin substudy of WHI reported that daily CE/MPA increased the risk of ovarian cancer. After an average follow-up of 5.6 years, the relative risk for ovarian cancer for CE/MPA versus placebo was 1.58 (95 percent nCI, 0.77–3.24) but was not statistically significant. The absolute risk for CE/MPA was 4.2 versus 2.7 cases per 10,000 women-years. In some epidemiologic studies, the use of estrogen-only products, in particular for 10 or more years, has been associated with an increased risk of ovarian cancer. Other epidemiologic studies have not found these associations.

3. Dementia

In the estrogen alone Women's Health Initiative Memory Study (WHIMS), a substudy of WHI, a population of 2,947 hysterectomized women aged 65 to 79 years was randomized to daily conjugated estrogens (CE 0.625 mg) or placebo. In the estrogen plus progestin WHIMS substudy, a population of 4,532 postmenopausal women aged 65 to 79 years was randomized to daily CE 0.625 mg plus medroxyprogesterone acetate (MPA 2.5 mg) or placebo.

In the estrogen alone substudy, after an average follow-up of 5.2 years, 28 women in the CE alone group and 19 women in the placebo group were diagnosed with probable dementia. The relative risk of probable dementia for estrogen CE alone versus placebo was 1.49 (95 percent CI, 0.83–2.66). The absolute risk of probable dementia for CE alone versus placebo was 37 versus 25 cases per 10,000 women-years. (See CLINICAL STUDIES and PRECAUTIONS, Geriatric Use.)

In the estrogen plus progestin substudy, after an average follow-up of 4 years, 40 women in the CE/MPA group and 21 women in the placebo group were diagnosed with probable dementia. The relative risk of probable dementia for CE/MPA versus placebo was 2.05 (95 percent CI, 1.21–3.48). The absolute risk of probable dementia for CE/MPA versus placebo was 45 versus 22 cases per 10,000 women-years. (See CLINICAL STUDIES and PRECAUTIONS, Geriatric Use.)

When data from the two populations were pooled as planned in the WHIMS protocol, the reported overall relative risk for probable dementia was 1.76 (95 percent CI, 1.19–2.60). Since both substudies were conducted in women aged 65 to 79 years, it is unknown whether these findings apply to younger postmenopausal women. (See BOXED WARNINGS and PRECAUTIONS, Geriatric Use.)

4. Gallbladder disease

A two- to four-fold increase in the risk of gallbladder disease requiring surgery in postmenopausal women receiving estrogens has been reported.

5. Hypercalcemia

Estrogen administration may lead to severe hypercalcemia in patients with breast cancer and bone metastases. If hypercalcemia occurs, use of the drug should be stopped and appropriate measures taken to reduce the serum calcium level.

6. Visual abnormalities

Retinal vascular thrombosis has been reported in patients receiving estrogens. Discontinue medication pending examination if there is sudden partial or complete loss of vision, or a sudden onset of proptosis, diplopia, or migraine. If examination reveals papilledema or retinal vascular lesions, estrogens should be discontinued.

PRECAUTIONS

A. General

1. Addition of a progestin when a woman has not had a hysterectomy

Studies of the addition of a progestin for 10 or more days of a cycle of estrogen administration, or daily with estrogen in a continuous regimen, have reported a lowered incidence of endometrial hyperplasia than would be induced by estrogen treatment alone. Endometrial hyperplasia may be a precursor to endometrial cancer.

There are, however, possible risks that may be associated with the use of progestins with estrogens compared to estrogen alone regimens. These include a possible increased risk of breast cancer, adverse effects on lipoprotein metabolism (lowering HDL, raising LDL), and impairment of glucose tolerance.

2. Elevated blood pressure

In a small number of case reports, substantial increases in blood pressure have been attributed to idiosyncratic reactions to estrogens. In a large, randomized, placebo-controlled clinical trial, a generalized effect of estrogen therapy on blood pressure was not seen. Blood pressure should be monitored at regular intervals with estrogen use.

3. Hypertriglyceridemia

In patients with preexisting hypertriglyceridemia, estrogen therapy may be associated with elevations of plasma triglycerides leading to pancreatitis and other complications. Consider discontinuation of treatment if pancreatitis or other complications develop.

4. Impaired liver function and past history of cholestatic jaundice

ESTRING vaginal ring should be used with caution in patients with impaired liver function. Estrogens may be poorly metabolized in patients with impaired liver function. For patients with a history of cholestatic jaundice associated with past estrogen use or with pregnancy, caution should be exercised and in the case of recurrence, medication should be discontinued.

5. Hypothyroidism

Estrogen administration leads to increased thyroid-binding globulin (TBG) levels. Patients with normal thyroid function can compensate for the increased TBG by making more thyroid hormone, thus maintaining free T4 and T3 serum concentrations in the normal range. Patients dependent on thyroid hormone replacement therapy who are also receiving estrogens may require increased doses of their thyroid replacement therapy. These patients should have their thyroid function monitored in order to maintain their free thyroid hormone levels in an acceptable range.

6. Hypocalcemia

Estrogens should be used with caution in individuals with severe hypocalcemia.

7. Fluid retention

Estrogens may cause some degree of fluid retention. Patients who have conditions that might be influenced by this factor, such as a cardiac or renal dysfunction, warrant careful observation when estrogens are prescribed.

8. Exacerbation of endometriosis

Endometriosis may be exacerbated with administration of estrogens. A few cases of malignant transformation of residual endometrial implants have been reported in women treated post-hysterectomy with estrogen alone therapy. For patients known to have residual endometriosis post-hysterectomy, the addition of progestin should be considered.

9. Exacerbation of other conditions

Estrogens may cause an exacerbation of asthma, diabetes mellitus, epilepsy, migraine or porphyria, systemic lupus erythematosus, and hepatic hemangiomas and should be used with caution in women with these conditions.

10. Location of ESTRING

Some women have experienced moving or gliding of ESTRING within the vagina. Instances of ESTRING being expelled from the vagina in connection with moving the bowels, strain, or constipation have been reported. If this occurs, ESTRING can be rinsed in lukewarm water and reinserted into the vagina by the patient.

11. Vaginal Irritation

ESTRING may not be suitable for women with narrow, short, or stenosed vaginas. Narrow vagina, vaginal stenosis, prolapse, and vaginal infections are conditions that make the vagina more susceptible to ESTRING-caused irritation or ulceration. Women with signs or symptoms of vaginal irritation should alert their physician.

12. Vaginal Infection

Vaginal infection is generally more common in postmenopausal women due to the lack of the normal flora of fertile women, especially lactobacillus, and the subsequent higher pH. Vaginal infections should be treated with appropriate antimicrobial therapy before initiation of ESTRING. If a vaginal infection develops during use of ESTRING, then ESTRING should be removed and reinserted only after the infection has been appropriately treated.

B. Information for the Patient

Physicians are advised to discuss the PATIENT INFORMATION leaflet with patients for whom they prescribe ESTRING.

C. Laboratory Tests

Serum follicle stimulating hormone and estradiol levels have not been shown to be useful in the management of moderate to severe symptoms of vulvar and vaginal atrophy.

D. Drug and Laboratory Test Interactions

1. Accelerated prothrombin time, partial thromboplastin time, and platelet aggregation time; increased platelet count; increased factors II, VII antigen, VIII antigen, VIII coagulant activity, IX, X, XII, VII-X complex, II-VII-X complex, and beta-thromboglobulin; decreased levels of anti-factor Xa and antithrombin III, decreased antithrombin III activity; increased levels of fibrinogen and fibrinogen activity; increased plasminogen antigen and activity.
2. Increased thyroid-binding globulin (TBG) levels leading to increased circulating total thyroid hormone levels, as measured by protein-bound iodine (PBI), T4 levels (by column or by radioimmunoassay) or T3 levels by radioimmunoassay. T3 resin uptake is decreased, reflecting the elevated TBG. Free T4 and free T3 concentrations are unaltered. Patients on thyroid replacement therapy may require higher doses of thyroid hormone.
3. Other binding proteins may be elevated in serum, (i.e., corticosteroid binding globulin [CBG], sex hormone-binding globulin [SHBG]), leading to increased circulating corticosteroid and sex steroids, respectively. Free hormone concentrations may be decreased. Other plasma proteins may be increased (angiotensinogen/renin substrate, alpha-1-antitrypsin, ceruloplasmin).
4. Increased plasma HDL and HDL2 cholesterol subfraction concentrations, reduced LDL cholesterol concentration, increased triglycerides levels.
5. Impaired glucose tolerance.

E. Carcinogenesis, Mutagenesis, and Impairment of Fertility

Long-term continuous administration of natural and synthetic estrogens in certain animal species increases the frequency of carcinomas of the breast, uterus, cervix, vagina, testes and liver.

F. Pregnancy

ESTRING should not be used during pregnancy. (See CONTRAINDICATIONS.)

There appears to be little or no increased risk of birth defects in children born to women who have used estrogens and progestins as an oral contraceptive inadvertently during early pregnancy.

G. Nursing Mothers

ESTRING should not be used during lactation. Estrogen administration to nursing mothers has been shown to decrease the quantity and quality of the breast milk. Detectable amounts of estrogens have been identified in the milk of mothers receiving this drug.

H. Pediatric Use

ESTRING is not indicated for pediatric use and no clinical data have been collected in children.

I. Geriatric Use

There have not been sufficient numbers of geriatric patients involved in studies utilizing ESTRING to determine whether those over 65 years of age differ from younger subjects in their response to ESTRING.

In the estrogen alone substudy of the Women's Health Initiative (WHI) study, 46 percent (n = 4,943) of subjects were 65 years of age and older, while 7.1 percent (n = 767) of subjects were 75 years of age and older. There was a higher relative risk (daily CE 0.625 mg versus placebo) of stroke in women less than 75 years of age compared to women 75 years and older.

In the estrogen alone substudy of the Women's Health Initiative Memory Study (WHIMS), a substudy of WHI, a population of 2,947 hysterectomized women, aged 65 to 79 years of age, was randomized to receive daily conjugated estrogens (CE 0.625 mg daily) or placebo. After an average follow-up of 5.2 years, the relative risk (CE versus placebo) of probable dementia was 1.49 (95 percent CI, 0.83–2.66). The absolute risk of developing probable dementia with estrogen alone was 37 versus 25 cases per 10,000 women-years compared with placebo.

Of the total number of subjects in the estrogen plus progestin substudy of WHI, 44 percent (n = 7,320) were 65 years of age and older, while 6.6 percent (n = 1,095) were 75 years of age and older. In women 75 years of age and older compared to women less than 75 years of age, there was a higher relative risk of nonfatal stroke and invasive breast cancer in the estrogen plus progestin group versus placebo. In women greater than 75, the increased risk of nonfatal stroke and invasive breast cancer observed in the estrogen plus progestin group compared to placebo was 75 versus 24 per 10,000 women-years and 52 versus 12 per 10,000 women-years, respectively.

In the estrogen plus progestin WHIMS substudy, a population of 4,532 postmenopausal women, aged 65 to 79 years, was randomized to receive CE 0.625 mg/MPA 2.5 mg or placebo. In the estrogen plus progestin group, after an average follow-up of 4 years, the relative risk (CE/MPA versus placebo) of probable dementia was 2.05 (95 percent CI, 1.21–3.48). The absolute risk of developing probable dementia with CE/MPA was 45 versus 22 cases per 10,000 women-years compared with placebo.

Seventy-nine percent of the cases of probable dementia occurred in women that were older than 70 for the CE alone group, and 82 percent of the cases of probable dementia occurred in women who were older than 70 in the CE/MPA group. The most common classification of probable dementia in both the treatment groups and placebo groups was Alzheimer's disease.

When data from the two populations were pooled as planned in the WHIMS protocol, the reported overall relative risk for probable dementia was 1.76 (95 percent CI, 1.19–2.60). Since both substudies were conducted in women aged 65 to 79 years, it is unknown whether these findings apply to younger postmenopausal women. (See BOXED WARNINGS and WARNINGS, Dementia.)

ADVERSE REACTIONS

See BOXED WARNINGS, WARNINGS and PRECAUTIONS

Because clinical trials are conducted under widely varying conditions, adverse reaction rates observed in the clinical trials of a drug cannot be directly compared to rates in the clinical trials of another drug and may not reflect the rates observed in practice.

In the two pivotal controlled studies, discontinuation of treatment due to an adverse event was required by 5.4 percent of patients receiving ESTRING and 3.9 percent of patients receiving conjugated estrogens vaginal cream. The most common reasons for withdrawal from ESTRING treatment due to an adverse event were vaginal discomfort and gastrointestinal symptoms.

The adverse events reported with a frequency of 3 percent or greater in the two pivotal controlled studies by patients receiving ESTRING or conjugated estrogens vaginal cream are listed in Table 4.

Table 4: Adverse Events Reported by 3 Percent or More of Patients Receiving Either ESTRING or Conjugated Estrogens Vaginal Cream in Two Pivotal Controlled Studies
ADVERSE EVENT | ESTRING (n = 257) % | Conjugated Estrogens Vaginal Cream (n = 129) %
Musculoskeletal
Back Pain | 6 | 8
Arthritis | 4 | 2
Arthralgia | 3 | 5
Skeletal Pain | 2 | 4
CNS/Peripheral Nervous System
Headache | 13 | 16
Psychiatric
Insomnia | 4 | 0
Gastrointestinal
Abdominal Pain | 4 | 2
Nausea | 3 | 2
Respiratory
Upper Respiratory Tract Infection | 5 | 6
Sinusitis | 4 | 3
Pharyngitis | 1 | 3
Urinary
Urinary Tract Infection | 2 | 7
Female Reproductive
Leukorrhea | 7 | 3
Vaginitis | 5 | 2
Vaginal Discomfort/Pain | 5 | 5
Vaginal Hemorrhage | 4 | 5
Asymptomatic Genital Bacterial Growth | 4 | 6
Breast Pain | 1 | 7
Resistance Mechanisms
Genital Moniliasis | 6 | 7
Body as a Whole
Flu-Like Symptoms | 3 | 2
Hot Flushes | 2 | 3
Allergy | 1 | 4
Miscellaneous
Family Stress | 2 | 3

Other adverse events (listed alphabetically) occurring at a frequency of 1 to 3 percent in the two pivotal controlled studies by patients receiving ESTRING include: anxiety, bronchitis, chest pain, cystitis, dermatitis, diarrhea, dyspepsia, dysuria, flatulence, gastritis, genital eruption, urogenital pruritus, hemorrhoids, leg edema, migraine, otitis media, skin hypertrophy, syncope, toothache, tooth disorder, urinary incontinence.

Post-Marketing Experience

1. A few cases of toxic shock syndrome (TSS) have been reported in women using vaginal rings. TSS is a rare, but serious disease that may cause death. Warning signs of TSS include fever, nausea, vomiting, diarrhea, muscle pain, dizziness, faintness, or a sunburn-rash on face and body.
2. A few cases of ring adherence to the vaginal wall, making ring removal difficult, have been reported. Vaginal wall ulceration or erosion should be carefully evaluated. If an ulceration or erosion has occurred, consideration should be given to leaving the ring out and not replacing it until healing is complete in order to prevent the ring from adhering to the healing tissue.
3. A few cases of bowel obstruction and vaginal ring use have been reported. Persistent abdominal complaints consistent with obstruction should be carefully evaluated.

The following additional adverse events were reported at least once by patients receiving ESTRING in the worldwide clinical program, which includes controlled and uncontrolled studies. A causal relationship with ESTRING has not been established.

Body as a Whole: allergic reaction

CNS/Peripheral Nervous System: dizziness

Gastrointestinal: enlarged abdomen, vomiting

Metabolic/Nutritional Disorders: weight decrease or increase

Musculoskeletal: arthropathy (including arthrosis)

Psychiatric: depression, decreased libido, nervousness

Reproductive: breast engorgement, breast enlargement, intermenstrual bleeding, genital edema, vulval disorder

Skin/Appendages: pruritus, pruritus ani

Urinary: micturition frequency, urethral disorder

Vascular: thrombophlebitis

Vision: abnormal vision

The following additional adverse reactions have been reported with estrogens:

Genitourinary system: abnormal uterine bleeding/spotting; dysmenorrheal/pelvic pain; increase in size of uterine leiomyomata; vaginitis, including vaginal candidiasis; change in amount of cervical secretion; changes in cervical ectropion; ovarian cancer; endometrial hyperplasia; endometrial cancer

Breasts: tenderness, enlargement, pain, nipple discharge, galactorrhea; fibrocystic breast changes; breast cancer

Cardiovascular: deep and superficial venous thrombosis; pulmonary embolism; thrombophlebitis; myocardial infarction; stroke; increase in blood pressure

Gastrointestinal: nausea, vomiting; abdominal cramps, bloating; cholestatic jaundice; increased incidence of gallbladder disease; pancreatitis, enlargement of hepatic hemangiomas

Skin: chloasma or melasma that may persist when drug is discontinued; erythema multiforme; erythema nodosum; hemorrhagic eruption; loss of scalp hair; hirsutism, rash

Eyes: retinal vascular thrombosis; intolerance to contact lenses

Central Nervous System: headache; migraine; dizziness; mental depression; exacerbation of chorea; nervousness; mood disturbances; irritability; exacerbation of epilepsy, dementia

Miscellaneous: increase or decrease in weight; glucose intolerance; aggravation of porphyria; edema; arthralgias; leg cramps; changes in libido; angioedema; anaphylactoid/anaphylactic reactions; hypocalcemia (preexisting condition); exacerbation of asthma; increased triglycerides

OVERDOSAGE

Overdosage of estrogen may cause nausea and vomiting, breast tenderness, abdominal pain, drowsiness/fatigue and withdrawal bleeding may occur in females. Treatment of overdose consists of discontinuation of ESTRING together with institution of appropriate symptomatic care.

DOSAGE AND ADMINISTRATION

One ESTRING (estradiol vaginal ring) is to be inserted as deeply as possible into the upper one-third of the vaginal vault. The ring is to remain in place continuously for three months, after which it is to be removed and, if appropriate, replaced by a new ring. The need to continue treatment should be assessed at 3 or 6 month intervals.

Should the ring be removed or fall out at any time during the 90-day treatment period, the ring should be rinsed in lukewarm water and re-inserted by the patient, or, if necessary, by a physician or nurse.

Retention of the ring for greater than 90 days does not represent overdosage but will result in progressively greater underdosage with the attendant risk of loss of efficacy and increasing risk of vaginal infections and/or erosions.

Instructions for Use

ESTRING (estradiol vaginal ring) insertion

The ring should be pressed into an oval and inserted into the upper third of the vaginal vault. The exact position is not critical. When ESTRING is in place, the patient should not feel anything. If the patient feels discomfort, ESTRING is probably not far enough inside. Gently push ESTRING further into the vagina.

ESTRING use

ESTRING should be left in place continuously for 90 days and then, if continuation of therapy is deemed appropriate, replaced by a new ESTRING.

The patient should not feel ESTRING when it is in place and it should not interfere with sexual intercourse. Straining at defecation may make ESTRING move down in the lower part of the vagina. If so, it may be pushed up again with a finger.

If ESTRING is expelled totally from the vagina, it should be rinsed in lukewarm water and reinserted by the patient (or doctor/nurse if necessary).

ESTRING removal

ESTRING may be removed by hooking a finger through the ring and pulling it out.

For patient instructions, see Patient Information.

HOW SUPPLIED

Each ESTRING (estradiol vaginal ring) is individually packaged in a heat-sealed rectangular pouch consisting of three layers, from outside to inside: polyester, aluminum foil, and low density polyethylene, respectively. The pouch is provided with a tear-off notch on one side.

NDC 54868-5538-0 ESTRING (estradiol vaginal ring) 2 mg - available in single packs.

STORAGE

Store at controlled room temperature 15° to 30° C (59° to 86° F).

Rx only

LAB-0082-5.0

August 2008

Relabeling of "Additional Barcode Label" by:
Physicians Total Care, Inc.
Tulsa, OK 74146

PATIENT INFORMATION

ESTRING
(estradiol vaginal ring)

Read this PATIENT INFORMATION before you start using ESTRING and read the patient information each time you refill your ESTRING prescription. There may be new information. This information does not take the place of talking to your healthcare provider about your menopausal symptoms and their treatment.

BOXED WARNING

What is the most important information I should know about ESTRING (an estrogen hormone)?

- Estrogens increase the chance of getting cancer of the uterus.

Report any unusual vaginal bleeding right away while you are using ESTRING. Vaginal bleeding after menopause may be a warning sign of cancer of the uterine (womb). Your healthcare provider should check any unusual vaginal bleeding to find out the cause.

- Do not use estrogens with or without progestins to prevent heart disease, heart attacks, strokes, or dementia.

Using estrogens with or without progestins may increase your chance of getting heart attacks, strokes, breast cancer, and blood clots. Using estrogens with or without progestins may increase your risk of dementia, based on a study of women age 65 years or older.

You and your healthcare provider should talk regularly about whether you still need treatment with ESTRING.

What is ESTRING?

ESTRING (estradiol vaginal ring) is an off-white, soft, flexible ring with a center that contains 2 mg of estradiol (an estrogen hormone). ESTRING releases estradiol into the vagina in a consistent, stable manner for 90 days. The soft, flexible ring is placed in the upper third of the vagina (by the physician or the patient). ESTRING should be removed after 90 days of continuous use. If continuation of therapy is indicated, the flexible ring should be replaced.

What is ESTRING used for?

ESTRING is used after menopause to:

- Treat moderate to severe itching, burning, and dryness in or around the vagina.

You and your healthcare provider should talk regularly about whether you still need treatment with ESTRING to control these problems.

Who should not use ESTRING?

Do not start using ESTRING if you:

- Have unusual vaginal bleeding
- Currently have or have had certain cancers
  Estrogens may increase the chance of getting certain types of cancers, including cancer of the breast or uterus. If you have or had cancer, talk with your healthcare provider about whether you should use ESTRING.
- Had a stroke or heart attack in the past year
- Currently have or have had blood clots
- Currently have or have had liver problems
- Are allergic to any of the ingredients in ESTRING
  See the list of ingredients in ESTRING at the end of this leaflet.
- Think you may be pregnant

Tell your healthcare provider:

- If you are breastfeeding
  The hormone in ESTRING can pass into your breast milk.
- About all of your medical problems
  Your healthcare provider may need to check you more carefully if you have certain conditions, such as asthma (wheezing), epilepsy (seizures), migraine, endometriosis, lupus, or problems with your heart, liver, thyroid, kidneys, or have high calcium levels in your blood.
- About all the medicines you take
  This includes prescription and nonprescription medicines, vitamins, and herbal supplements. Some medicines may affect how ESTRING works. ESTRING may also affect how your other medicines work.
- If you are going to have surgery or will be on bed rest
  You may need to stop taking estrogens.

How should I use ESTRING?

ESTRING is a local estrogen therapy designed to relieve itching, burning and dryness in and around the vagina . ESTRING PROVIDES RELIEF OF LOCAL SYMPTOMS OF MENOPAUSE ONLY.

Estrogens should be used only as long as needed. You and your healthcare provider should talk regularly (for example, every 3 to 6 months) about whether you still need treatment with ESTRING.

ESTRING INSERTION

ESTRING can be inserted and removed by you or your doctor or healthcare provider. To insert ESTRING yourself, choose the position that is most comfortable for you: standing with one leg up, squatting, or lying down.

1. After washing and drying your hands, remove ESTRING from its pouch using the tear-off notch on the side. (Since the ring becomes slippery when wet, be sure your hands are dry before handling it.)
2. Hold ESTRING between your thumb and index finger and press the opposite sides of the ring together as shown.
3. Gently push the compressed ring into your vagina as far as you can.

ESTRING PLACEMENT

The exact position of ESTRING is not critical, as long as it is placed in the upper third of the vagina.

When ESTRING is in place, you should not feel anything. If you feel uncomfortable, ESTRING is probably not far enough inside. Use your finger to gently push ESTRING further into your vagina.

There is no danger of ESTRING being pushed too far up in the vagina or getting lost. ESTRING can only be inserted as far as the end of the vagina, where the cervix (the narrow, lower end of the uterus) will block ESTRING from going any further (see diagram of Female Anatomy).

ESTRING USE

Once inserted, ESTRING should remain in place in the vagina for 90 days.

Most women and their partners experience no discomfort with ESTRING in place during intercourse, so it is NOT necessary that the ring be removed. If ESTRING should cause you or your partner any discomfort, you may remove it prior to intercourse (see ESTRING Removal, below). Be sure to reinsert ESTRING as soon as possible afterwards.

ESTRING may slide down into the lower part of the vagina as a result of the abdominal pressure or straining that sometimes accompanies constipation. If this should happen, gently guide ESTRING back into place with your finger.

There have been rare reports of ESTRING falling out in some women following intense straining or coughing. If this should occur, simply wash ESTRING with lukewarm (NOT hot) water and reinsert it.

ESTRING DRUG DELIVERY

Once in the vagina, ESTRING begins to release estradiol immediately. ESTRING will continue to release a low, continuous dose of estradiol for the full 90 days it remains in place.

It will take about 2 to 3 weeks to restore the tissue of the vagina and urinary tract to a healthier condition and to feel the full effect of ESTRING in relieving vaginal and urinary symptoms. If your symptoms persist for more than a few weeks after beginning ESTRING therapy, contact your doctor or healthcare provider.

One of the most frequently reported effects associated with the use of ESTRING is an increase in vaginal secretions. These secretions are like those that occur normally prior to menopause and indicate that ESTRING is working. However, if the secretions are associated with a bad odor or vaginal itching or discomfort, be sure to contact your doctor or healthcare provider.

ESTRING REMOVAL

After 90 days there will no longer be enough estradiol in the ring to maintain its full effect in relieving your vaginal or urinary symptoms. ESTRING should be removed at that time and replaced with a new ESTRING, if your doctor determines that you need to continue your therapy.

To remove ESTRING:

1. Wash and dry your hands thoroughly.
2. Assume a comfortable position, either standing with one leg up, squatting, or lying down.
3. Loop your finger through the ring and gently pull it out.
4. Discard the used ring in a waste receptacle. (Do not flush ESTRING.)

If you have any additional questions about removing ESTRING, contact your doctor or healthcare provider.

What are the possible side effects of ESTRING?

A few cases of toxic shock syndrome (TSS) have been reported in women using vaginal rings. Toxic shock syndrome is a rare but serious illness caused by a bacterial infection. If you have fever, nausea, vomiting, diarrhea, muscle pain, dizziness, faintness, or a sunburn-like rash on face and body, remove ESTRING and contact your healthcare provider. A few cases of the vaginal ring becoming attached to the vaginal wall, making ring removal difficult, have been reported.

The most frequently reported side effect with ESTRING use is increased vaginal secretions. Many of these vaginal secretions are like those that occur normally prior to menopause and indicate that ESTRING is working. Vaginal secretions that are associated with a bad odor, vaginal itching, or other signs of vaginal infection are NOT normal and may indicate a risk or a cause for concern. Other side effects may include vaginal discomfort, abdominal pain, or genital itching.

What are the possible side effects of estrogens ?

Side effects are grouped by how serious they are and how often they happen when you are treated.

Serious but less common side effects include:

- Breast cancer
- Cancer of the uterus
- Stroke
- Heart attack
- Blood clots
- Dementia
- Gallbladder disease
- Ovarian cancer
- High blood pressure
- Liver problems
- High blood sugar
- Enlargement of benign tumors of the uterus ("fibroids")
  Some of the warning signs of these serious side effects include:
  - Breast lumps
  - Unusual vaginal bleeding
  - Dizziness and faintness
  - Changes in speech
  - Severe headaches
  - Chest pain
  - Shortness of breath
  - Pains in your legs
  - Changes in vision
  - Vomiting
  - Yellowing of the skin, eyes or nail beds
    Call your healthcare provider right away if you get any of these warning signs, or any other unusual symptom that concerns you.

Less serious but common side effects include:

- Headache
- Breast pain
- Irregular vaginal bleeding or spotting
- Stomach/abdominal cramps, bloating
- Nausea and vomiting
- Hair loss
- Fluid retention
- Vaginal yeast infection

These are not all the possible side effects of estrogens. For more information, ask your healthcare provider or pharmacist.

What can I do to lower my chances of getting a serious side effect with ESTRING?

- Follow carefully the instructions for use.
- Talk with your healthcare provider regularly about whether you should continue using ESTRING.
- See your healthcare provider right away if you get vaginal bleeding while using ESTRING.
- If you have fever, nausea, vomiting, diarrhea, muscle pain, dizziness, faintness, or a sunburn-like rash on face and body, remove ESTRING and contact your healthcare provider.
- Contact your healthcare provider if you have difficulty removing the vaginal ring.
- Have a breast exam and mammogram (breast X-ray) every year unless your healthcare provider tells you something else. If members of your family have had breast cancer or if you have ever had breast lumps or an abnormal mammogram, you may need to have breast examinations more often.
- If you have high blood pressure, high cholesterol (fat in the blood), diabetes, are overweight, or if you use tobacco, you may have higher chances for getting heart disease. Ask your healthcare provider for ways to lower your chances for getting heart disease.

General information about safe and effective use of ESTRING

Medicines are sometimes prescribed for conditions that are not mentioned in patient information leaflets. Do not use ESTRING for conditions for which it was not prescribed. Do not give ESTRING to other people, even if they have the same symptoms you have. It may harm them.

Keep ESTRING out of the reach of children.

This leaflet provides a summary of the most important information about ESTRING. If you would like more information, talk with your healthcare provider or pharmacist. You can ask for information about ESTRING that is written for health professionals. You can get more information by calling the toll free number 1-888-691-6813.

What are the ingredients in ESTRING?

ESTRING (estradiol vaginal ring) is a slightly opaque ring with a whitish core containing a drug reservoir of 2 mg estradiol (an estrogen hormone). Estradiol, silicone polymers and barium sulfate are combined to form the ring.

Storage: Store at controlled room temperature 15° to 30° C (59° to 86° F).

LAB-0087-4.0

August 2008

PRINCIPAL DISPLAY PANEL - 2 mg Ring Carton

1 Unit
Rx only

Estring®
estradiol vaginal ring

2 mg